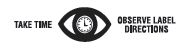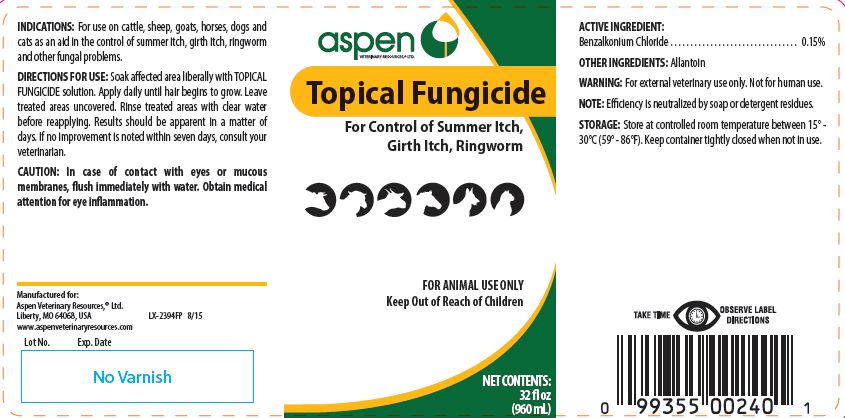 DRUG LABEL: Topical Fungicide
NDC: 46066-195 | Form: SOLUTION
Manufacturer: Aspen Veterinary
Category: animal | Type: OTC ANIMAL DRUG LABEL
Date: 20221105

ACTIVE INGREDIENTS: BENZALKONIUM CHLORIDE 3.09 mg/1 mL

Topical Fungicide

PURPOSE

For Control of Summer Itch, Girth Itch, Ringworm

KEEP OUT OF REACH OF CHILDREN

FOR ANIMAL USE ONLY
Keep Out of Reach of Children

INDICATIONS:

For use on cattle, sheep, goats, horses, dogs and cats as an aid in the control of summer itch, girth itch, ringworm and other fungal problems.

DIRECTIONS FOR USE:

Soak affected area liberally with TOPICAL FUNGICIDE solution. Apply daily until hair begins to grow. Leave treated areas uncovered. Rinse treated areas with clear water before reapplying. Results should be apparent in a matter of days. If no improvement is noted within seven days, consult your veterinarian.

CAUTION:

In case of contact with eyes or mucous membranes, flush immediately with water. Obtain medical attention for eye inflammation.

ACTIVE INGREDIENT:

Benzalkonium Chloride . . . . . . . . . . . . . . . . . . . . . . . . . . . . . . . . 0.15%

OTHER INGREDIENTS:

Allantoin

WARNING:

For external veterinary use only. Not for human use.

NOTE:

Efficiency is neutralized by soap or detergent residues.

STORAGE:

Store at controlled room temperature between 15° - 30°C (59° - 86°F). Keep container tightly closed when not in use.

NET CONTENTS:

32 fl oz (960 mL)

INFORMATION FOR OWNERS/CAREGIVERS

Manufactured for:
Aspen Veterinary Resources,® Ltd.
Liberty, MO 64068, USA LX-2394FP 8/15
www.aspenveterinaryresources.com